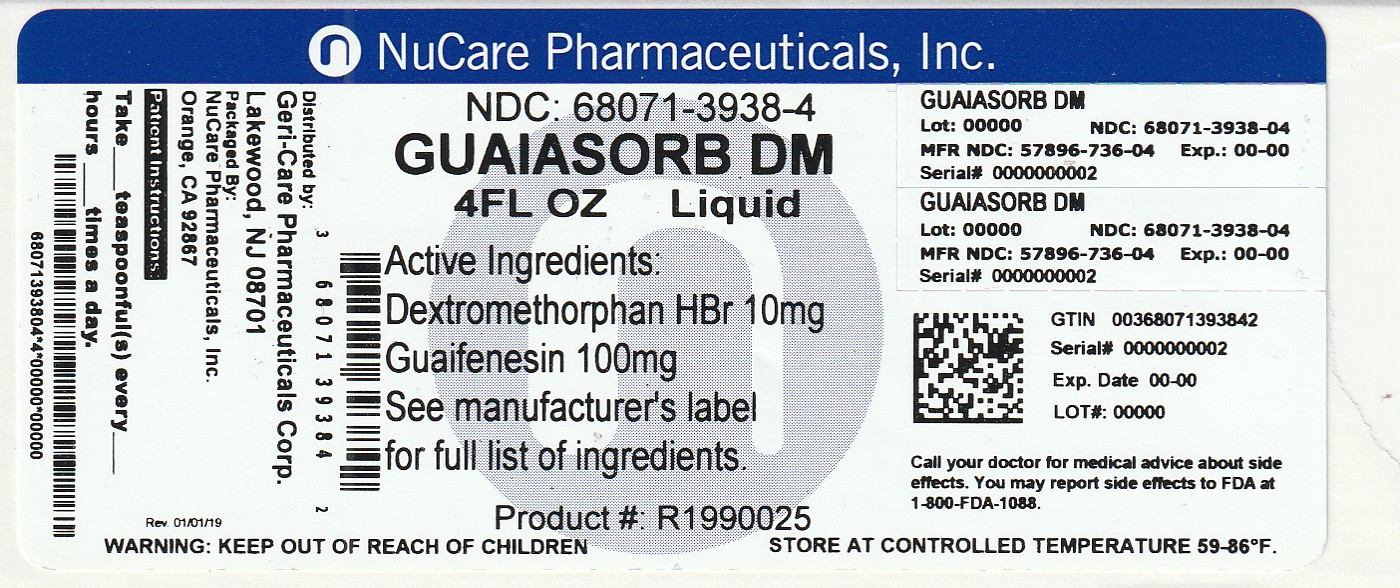 DRUG LABEL: Guaiasorb
NDC: 68071-3938 | Form: LIQUID
Manufacturer: NuCare Pharmaceuticals, Inc.
Category: otc | Type: HUMAN OTC DRUG LABEL
Date: 20251223

ACTIVE INGREDIENTS: DEXTROMETHORPHAN HYDROBROMIDE 10 mg/5 mL; GUAIFENESIN 100 mg/5 mL
INACTIVE INGREDIENTS: ANHYDROUS CITRIC ACID; MENTHOL; METHYLPARABEN; PROPYLENE GLYCOL; PROPYLPARABEN; WATER; SODIUM CITRATE; SUCRALOSE

GeriCare-GuaiasorbDM 736

Active ingredients (per 5 mL teaspoonful)

Dextromethorphan HBr 10 mg

Guaifenesin 100 mg

Purpose

- cough suppressant
- expectorant

Uses

- temporarily relieves cough due to minor throat and bronchial irritation
- helps loosen phlegm mucus
- helps thin bronchial secretions to make coughs more productive

Warnings

Do not use if you are now taking prescription monoamine oxidase inhibitor (MAOI) (certain drugs for depression, psychiatric or emotional conditions, or Parkinson's disease), or for 2 weeks after stopping the MAOI drug. If you do not know if your prescription drug contains an MAOI, ask a doctor or pharmacist before taking this product.

Ask a doctor before use if you have

- a cough with too much phlegm (mucus)
- a cough that lasts or is chronic such as occurs with smoking, asthma, chronic bronchitis, or emphysema.

Stop use and ask a doctor if cough lasts more than 7 days, comes back, or is accompanied by fever, rash, or headache that lasts. These could be signs of a serious condition

PREGNANCY OR BREAST FEEDING

If pregnant or breast-feeding, ask a health professional before use.

Keep out of reach of children. In case of overdose, get medical help or contact a Poison Control Center right away.

Directions

- do not exceed recommended dose
- take every 4 hours as needed, or as directed by a doctor
- do not take more than 6 doses in 24 hours

Adults and children 12 years and over | 2 teaspoonfuls (10 mL)
Children under 12 years | Do not use

INACTIVE INGREDIENT

Inactive ingreadients artificial and natural cherry flavor, citric acid, menthol, methylparaben, propylene glycol, propylparaben, purified water, sodium citrate, sucralose